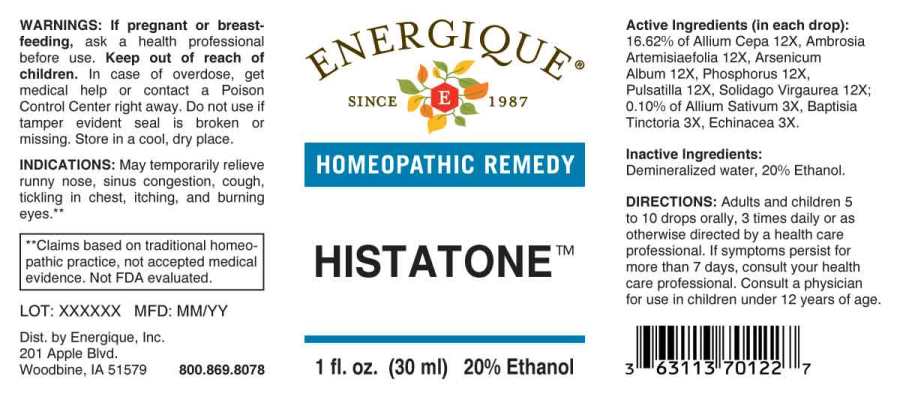 DRUG LABEL: Histatone
NDC: 44911-0580 | Form: LIQUID
Manufacturer: Energique, Inc.
Category: homeopathic | Type: HUMAN OTC DRUG LABEL
Date: 20241025

ACTIVE INGREDIENTS: GARLIC 3 [hp_X]/1 mL; BAPTISIA TINCTORIA ROOT 3 [hp_X]/1 mL; ECHINACEA ANGUSTIFOLIA WHOLE 3 [hp_X]/1 mL; ONION 12 [hp_X]/1 mL; AMBROSIA ARTEMISIIFOLIA WHOLE 12 [hp_X]/1 mL; ARSENIC TRIOXIDE 12 [hp_X]/1 mL; PHOSPHORUS 12 [hp_X]/1 mL; PULSATILLA PRATENSIS WHOLE 12 [hp_X]/1 mL; SOLIDAGO VIRGAUREA FLOWERING TOP 12 [hp_X]/1 mL
INACTIVE INGREDIENTS: WATER; ALCOHOL

DRUG FACTS:

ACTIVE INGREDIENTS:

(in each drop): 16.62% of Allium Cepa 12X, Ambrosia Artemisiaefolia 12X, Arsenicum Album 12X, Phosphorus 12X, Pulsatilla (Pratensis) 12X, Solidago Virgaurea 12X; 0.10% of Allium Sativum 3X, Baptisia Tinctoria 3X, Echinacea (Angustifolia) 3X.

INDICATIONS:

For temporary relief of hay fever, sinus, cough, bronchial irritation, itching and burning.**

**These statements are based upon traditional homeopathic practice. They have not been reviewed by the Food and Drug Administration.

WARNINGS:

If pregnant or breast-feeding, ask a health professional before use.

Keep out of reach of children. In case of overdose, get medical help or contact a Poison Control Center right away.

Do not use if tamper evident seal is broken or missing. Store in a cool, dry place.

Keep out of reach of children. In case of overdose, get medical help or contact a Poison Control Center right away.

DIRECTIONS:

Adults and children 5 to 10 drops orally, 3 times daily or as otherwise directed by a health care professional. If symptoms persist, consult your health care professional. Consult a physician for use in children under 12 years of age.

INDICATIONS:

For temporary relief of hay fever, sinus, cough, bronchial irritation, itching and burning.**

**These statements are based upon traditional homeopathic practice. They have not been reviewed by the Food and Drug Administration.

INACTIVE INGREDIENTS:

Demineralized water, 20% Ethanol

QUESTIONS:

Dist. by Energique, Inc.

201 Apple Blvd

Woodbine, IA 51579 800.869.8078

PACKAGE LABEL DISPLAY:

ENERGIQUE

SINCE 1987

HOMEOPATHIC REMEDY

HISTATONE

1 fl. oz. (30 ml)